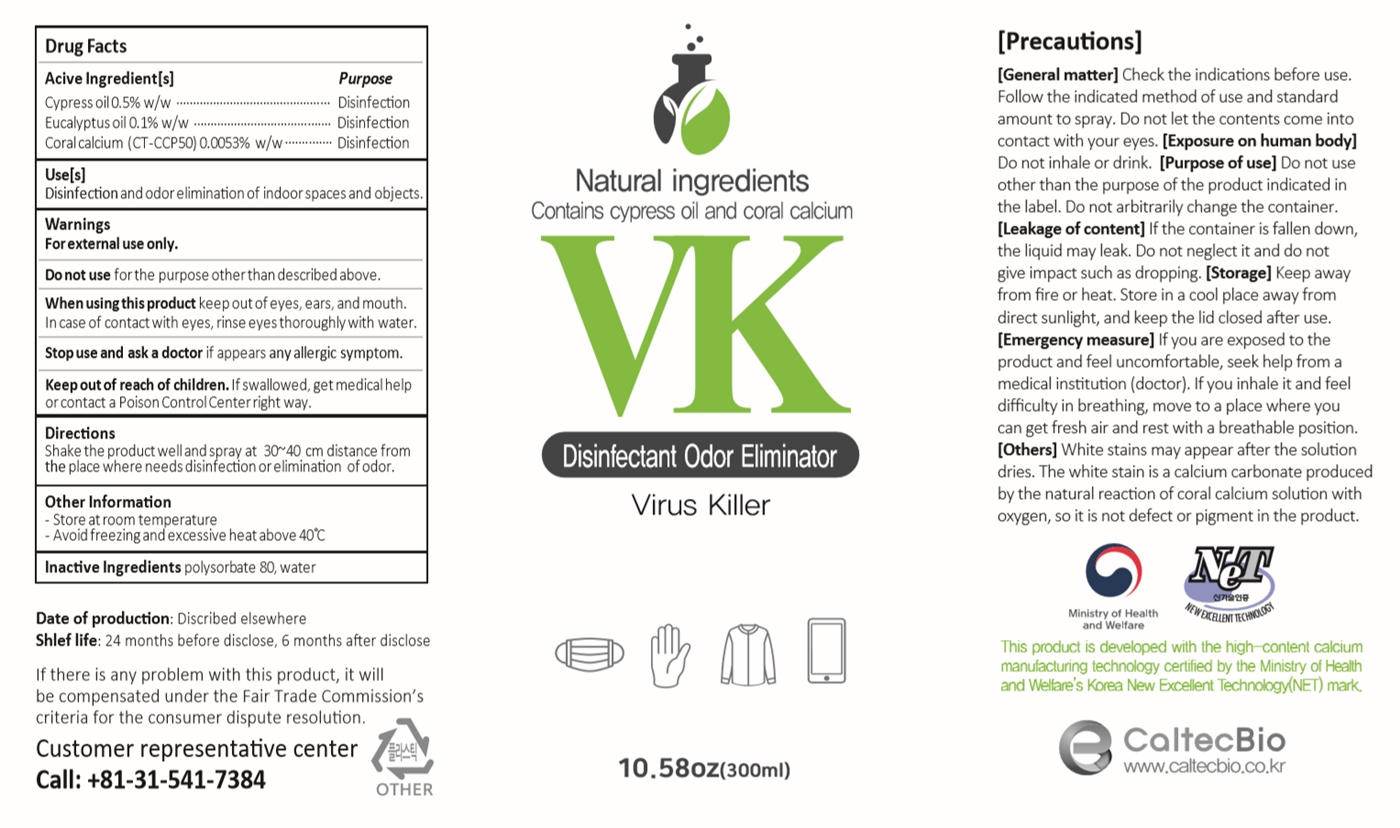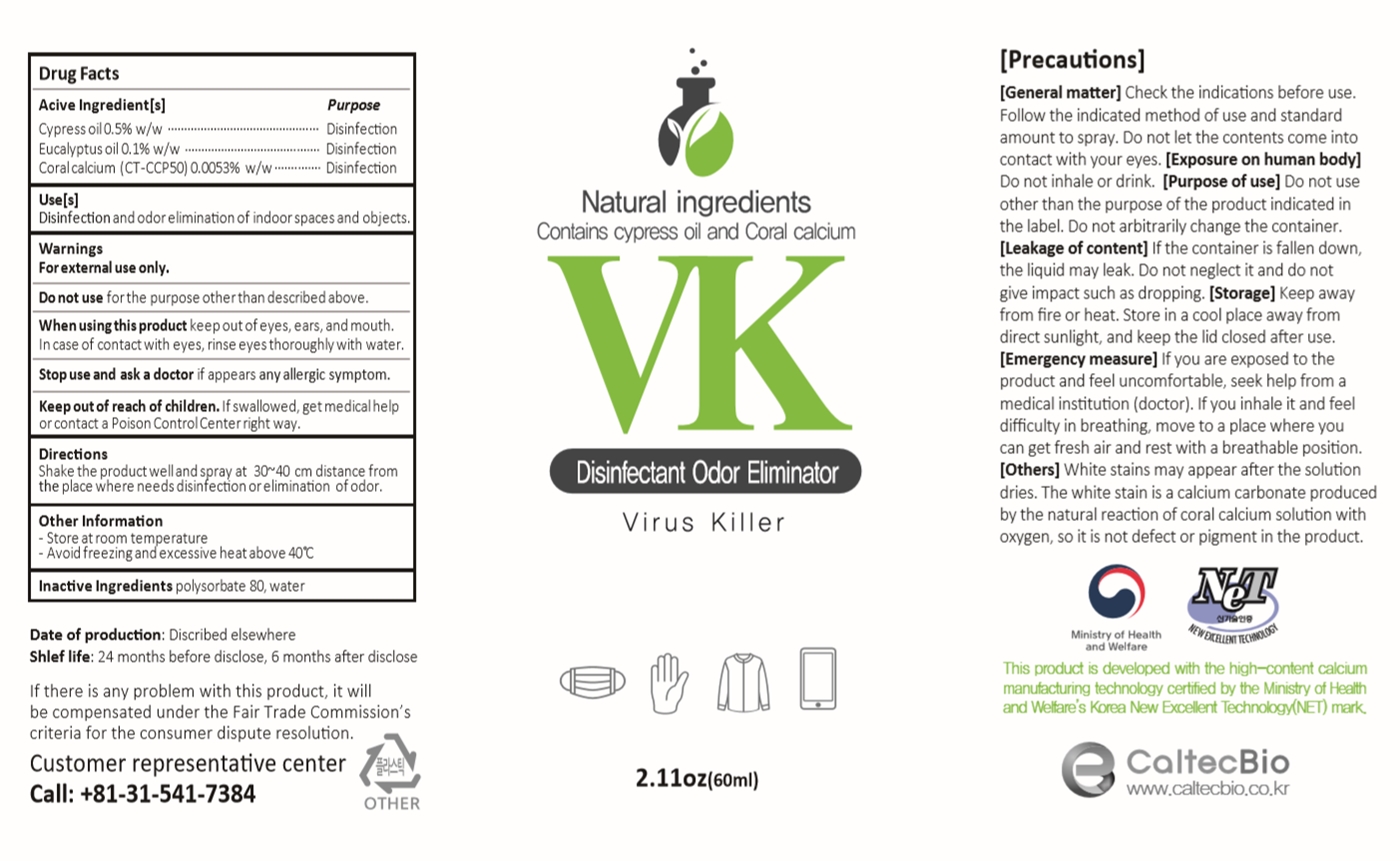 DRUG LABEL: VK
NDC: 77083-201 | Form: LIQUID
Manufacturer: CaltecBio Co., Ltd
Category: otc | Type: HUMAN OTC DRUG LABEL
Date: 20200430

ACTIVE INGREDIENTS: CALCIUM HYDROXIDE 0.0053 g/100 mL; EUCALYPTUS OIL 0.1 g/100 mL; CUPRESSUS SEMPERVIRENS LEAF OIL 0.5 g/100 mL
INACTIVE INGREDIENTS: WATER 98.7947 mL/100 mL; POLYSORBATE 80 0.6 mL/100 mL

Acive Ingredient[s]

Cypress oil 0.5%

Eucalyptus oil 0.1%

Coral calcium (CT-CCP50) 0.0053%

Purpose

Disinfection

Use[s]

Disinfection and odor elimination of indoor spaces and objects.

Warnings

For external use only.

Do not use

for the purpose other than described above.

When using this product

keep out of eyes, ears, and mouth. In case of contact with eyes, rinse eyes thoroughly with water.

Stop use and ask a doctor

if appears any allergic symptom.

Keep out of reach of children.

If swallowed, get medical help or contact a Poison Control Center right way.

Directions

Shake the product well and spray at 30~40 cm distance from the place where needs disinfection or elimination of odor.

Other Information

- Store at room temperature

- Avoid freezing and excessive heat above 40C

Inactive Ingredients

polysorbate80, water

[Precautions]

[General matter] Check the indications before use. Follow the indicated method of use and standard amount to spray. Do not let the contents come into contact with your eyes.

[Exposure on human body] Do not inhale or drink.

[Purpose of use] Do not use other than the purpose of the product indicated in the label. Do not arbitrarily change the container.

[Leakage of content] If the container is fallen down, the liquid may leak. Do not neglect it and do not give impact such as dropping.

[Storage] Keep away from ﬁre or heat. Store in a cool place away from direct sunlight, and keep the lid closed after use.

[Emergency measure] If you are exposed to the product and feel uncomfortable, seek help from a medical institution (doctor). If you inhale it and feel diﬃculty in breathing, move to a place where you can get fresh air and rest with a breathable position.

[Others] White stains may appear after the solution dries. The white stain is a calcium carbonate produced by the natural reaction of coral calcium solution with oxygen, so it is not defect or pigment in the product.